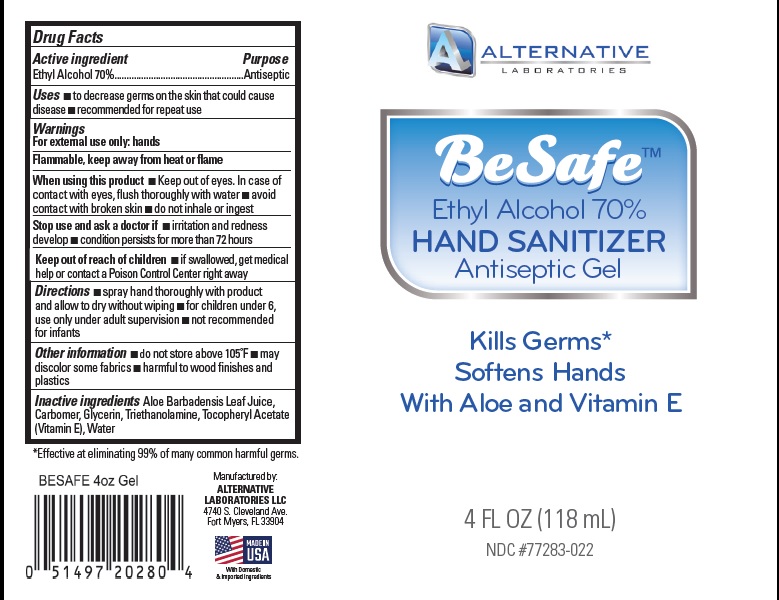 DRUG LABEL: Besafe Hand Sanitizer Gel
NDC: 72283-022 | Form: LIQUID
Manufacturer: Alternative Laboratories LLC
Category: otc | Type: HUMAN OTC DRUG LABEL
Date: 20221114

ACTIVE INGREDIENTS: ALCOHOL 70 mL/100 mL
INACTIVE INGREDIENTS: ALOE VERA LEAF; WATER; GLYCERIN; .ALPHA.-TOCOPHEROL ACETATE; CARBOMER HOMOPOLYMER, UNSPECIFIED TYPE; TROLAMINE

Active Ingredient

Ethyl Alcohol 70% v/v.

Purpose

Antiseptic

Uses

To decrease bacteria on the skin that could cause disease. recommended for repeated use.

Warnings

For external use only: hands
Flamable, keep away from heat or flame

When using this product keep out of eyes.In case of contact with eyes, flush throughly with water. Avoid contact with broken skin. Do not inhale or ingest

Stop use and ask a doctor if irritation and redness develop condition persists for more than 72 hours

Keep out of reach of children. If swallowed, get medical help or contact a Poison Control Center right away.

Directions:

spray hands throughly with product and allow to dry without wiping. For children under 6, use only under adult supervision. Not recommended for infants.

Other information: do not store above 105°F may discolor some fabrics. harmful to wood finishes and plastics.

Inactive ingredients

Aloe barbadensis leaf juice, Carbomer, Glycerin, Triethanolamine, tocopheryl acetate (Vitamin E), Water